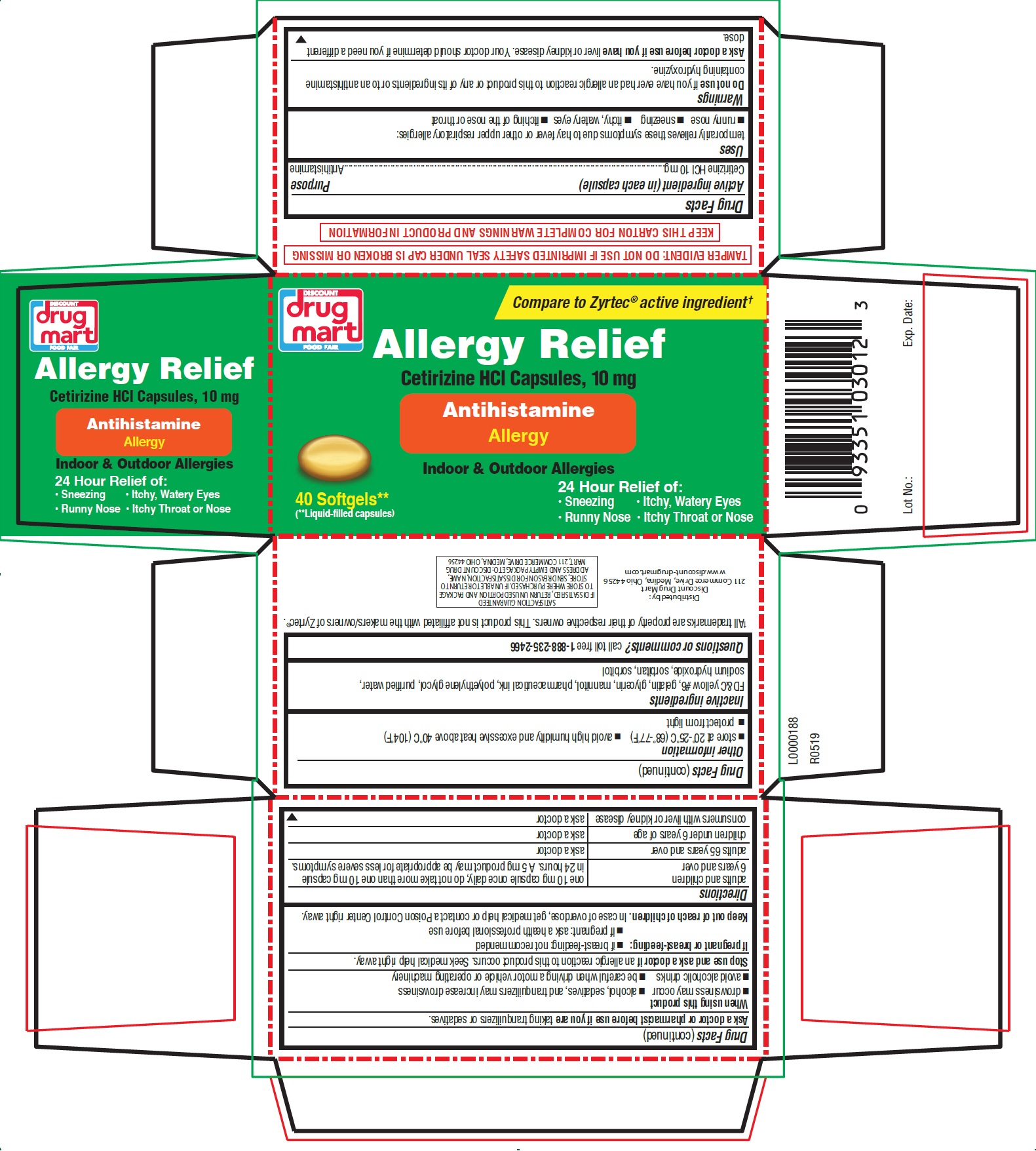 DRUG LABEL: Allergy Relief
NDC: 53943-219 | Form: CAPSULE
Manufacturer: DISCOUNT DRUG MART, INC.
Category: otc | Type: HUMAN OTC DRUG LABEL
Date: 20221229

ACTIVE INGREDIENTS: CETIRIZINE HYDROCHLORIDE 10 mg/1 1
INACTIVE INGREDIENTS: FD&C YELLOW NO. 6; GELATIN; GLYCERIN; MANNITOL; POLYETHYLENE GLYCOL, UNSPECIFIED; WATER; SODIUM HYDROXIDE; SORBITAN; SORBITOL

Drug Facts

Active ingredient (in each capsule)

Cetirizine HCl 10 mg

Purpose

Antihistamine

Uses

temporarily relieves these symptoms due to hay fever or other upper respiratory allergies:

- runny nose
- sneezing
- itchy, watery eyes
- itching of the nose or throat

Warnings

Do not use

if you have ever had an allergic reaction to this product or any of its ingredients or to an antihistamine containing hydroxyzine.

Ask a doctor before use if you have

liver or kidney disease. Your doctor should determine if you need a different dose.

Ask a doctor or pharmacist before use if you are

taking tranquilizers or sedatives.

When using this product

- drowsiness may occur
- alcohol, sedatives, and tranquilizers may increase drowsiness
- avoid alcoholic drinks
- be careful when driving a motor vehicle or operating machinery

Stop use and ask a doctor if

an allergic reaction to this product occurs. Seek medical help right away.

If pregnant or breast-feeding:

- if breast-feeding: not recommended
- if pregnant: ask a health professional before use

Keep out of reach of children.

In case of overdose, get medical help or contact a Poison Control Center right away.

Directions

adults and children 6 years and over | one 10 mg capsule once daily; do not take more than one 10 mg capsule in 24 hours. A 5 mg product may be appropriate for less severe symptoms.
adults 65 years and over | ask a doctor
children under 6 years of age | ask a doctor
consumers with liver or kidney disease | ask a doctor

Other information

- store at 20º-25ºC (68º-77ºF)
- avoid high humidity and excessive heat above 40ºC (104ºF)
- protect from light

Inactive ingredients

FD&C yellow #6, gelatin, glycerin, mannitol, pharmaceutical ink, polyethylene glycol, purified water, sodium hydroxide, sorbitan, sorbitol

Questions or comments?

call toll free 1-888-235-2466

TAMPER EVIDENT: DO NOT USE IF IMPRINTED SAFETY SEAL UNDER CAP IS BROKEN OR MISSING

KEEP THIS CARTON FOR COMPLETE WARNINGS AND PRODUCT INFORMATION

†All trademarks are property of their respective owners. This product is not affiliated with the makers/owners of Zyrtec®.

Distributed by:

Discount Drug Mart

211 Commerce Drive, Medina, Ohio 44256

www.discount-drugmart.com

SATISFACTION GUARANTEED

IF DISSATISFIED, RETURN UNUSED PORTION AND PACKAGE TO STORE WHERE PURCHASED. IF UNABLE TO RETURN TO STORE, SEND REASON FOR DISSATISFACTION, NAME, ADDRESS AND EMPTY PACKAGE TO: DISCOUNT DRUG MART, 211 COMMERCE DRIVE, MEDINA OHIO 44256

L0000188

R0519

Principal Display Panel

Compare to Zyrtec® active ingredient†

Allergy Relief

Cetirizine HCl Capsules, 10 mg

Antihistamine

Allergy

Indoor & Outdoor Allergies

24 Hour Relief of:

- Sneezing
- Runny Nose
- Itchy, Watery Eyes
- Itchy Throat or Nose

40 Softgels**

(**Liquid-filled capsules)